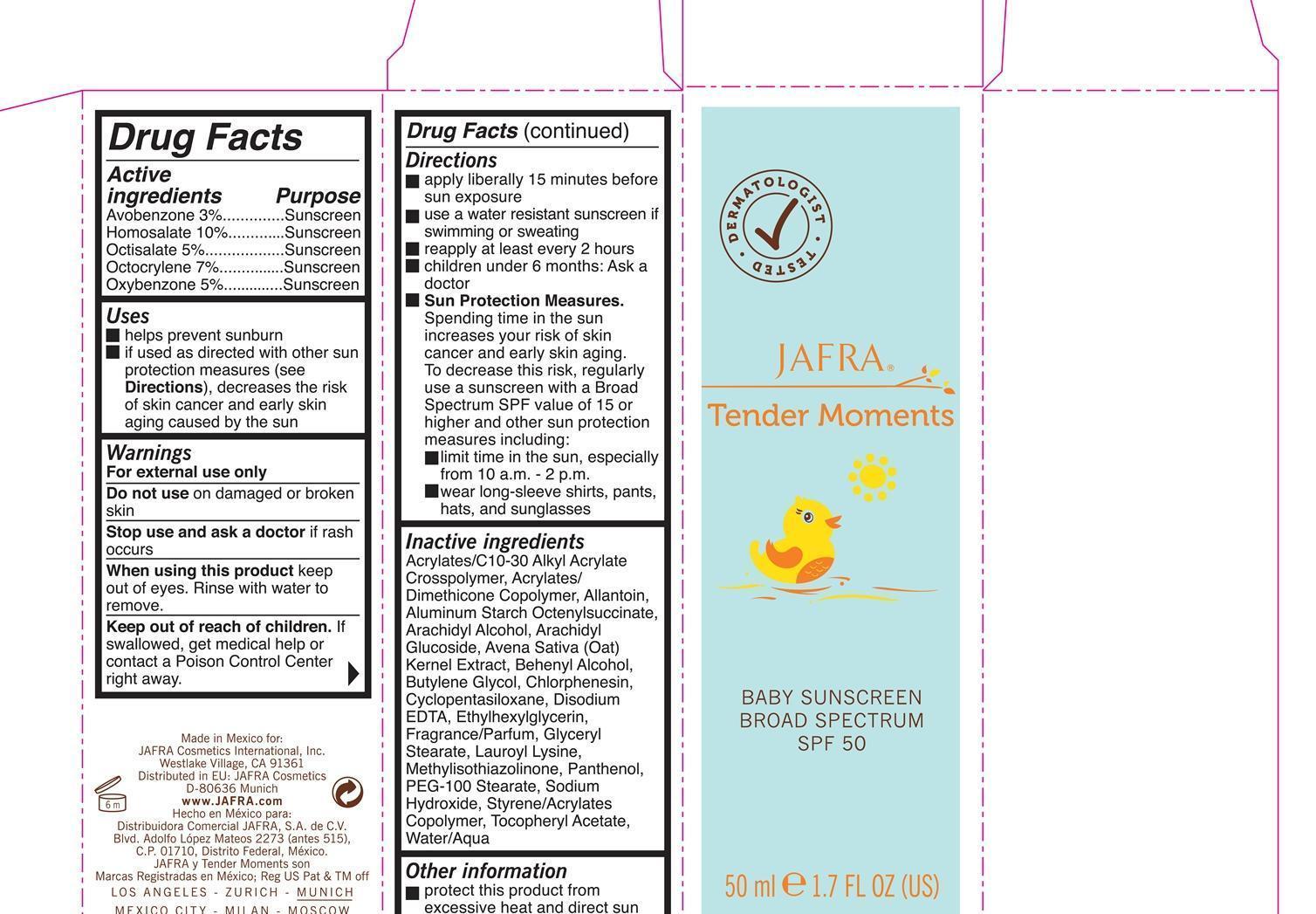 DRUG LABEL: Tender Moments Baby Sunscreen Broad Spectrum SPF 50

NDC: 68828-177 | Form: LIQUID
Manufacturer: JAFRA COSMETICS INTERNATIONAL
Category: otc | Type: HUMAN OTC DRUG LABEL
Date: 20200622

ACTIVE INGREDIENTS: AVOBENZONE 3 g/100 mL; HOMOSALATE 10 g/100 mL; OCTISALATE 5 g/100 mL; OCTOCRYLENE 7 g/100 mL; OXYBENZONE 5 g/100 mL
INACTIVE INGREDIENTS: ALLANTOIN; ALUMINUM STARCH OCTENYLSUCCINATE; ARACHIDYL ALCOHOL; ARACHIDYL GLUCOSIDE; OAT; DOCOSANOL; BUTYLENE GLYCOL; CHLORPHENESIN; CYCLOMETHICONE 5; EDETATE DISODIUM; ETHYLHEXYLGLYCERIN; GLYCERYL MONOSTEARATE; LAUROYL LYSINE; METHYLISOTHIAZOLINONE; PANTHENOL; PEG-100 STEARATE; SODIUM HYDROXIDE; .ALPHA.-TOCOPHEROL ACETATE; WATER

Tender Moments Baby Sunscreen

Active ingredients Purpose

Avobenzone 3% Sunscreen

Homosalate 10% Sunscreen

Octisalate 5% Sunscreen

Octocrylene 7% Sunscreen

Oxybenzone 5% Sunscreen

Uses

-helps prevent sunburn

-if used as directed with other sun protection measures (see Directions), decreases the risk of skin cancer and early skin aging by the sun.

Keep out of reach of children. If swallowed get medical help or contact a Poison Control Center right away.

Do not use on damaged or broken skin

Stop use and ask a doctor if rash occurs.

Warnings

For external use only

When using this product keep out of eyes. Rinse with water to remove.

Directions

apply liberally 15 minutes before sun exposure

use a water resistant sunscreen if swimming or sweating

reapply at least every 2 hours

children under 6 months: Ask a doctor

Sun Protection Measures

Spending time in the sun increases your risk of skin cancer and early skin aging. To decrease this risk, regularly use a sunscreen with a Broad Spectrum SPF value of 15 or higher and other sun protection measures including:

limit time in the sun, especially from 10 a.m.-2 p.m.

wear long-sleeve shirts, pants , hats, and sunglasses.

Inactive ingredients

Acrylates/C10-30 Alkyl Acrylate Crosspolymer, Acrylates/Dimethicone Copolymer, Allantoin, Aluminum Starch Octenylsuccinate, Arachidyl Alcohol, Arachidyl Glucoside, Avena Sativa (Oat) Kernel Extract, Behenyl Alcohol, Butylene Glycol, Chlorphenesin, Cyclopentasiloxane, Disodium EDTA, Ethylhexylglycerin, Fragrance/Parfum, Glyceryl Stearate, Lauroyl Lysine, Methylisothiazolinone, Panthenol, PEG-100 Stearate, Sodium Hydroxide, Styrene/Acrylates Copolymer, Tocopheryl Acetate, Water/Aqua.

PACKAGE LABEL

Jafra

Tender Moments

Baby Sunscreen Broad Spectrum SPF 50

50 ml 1.7 Fl Oz